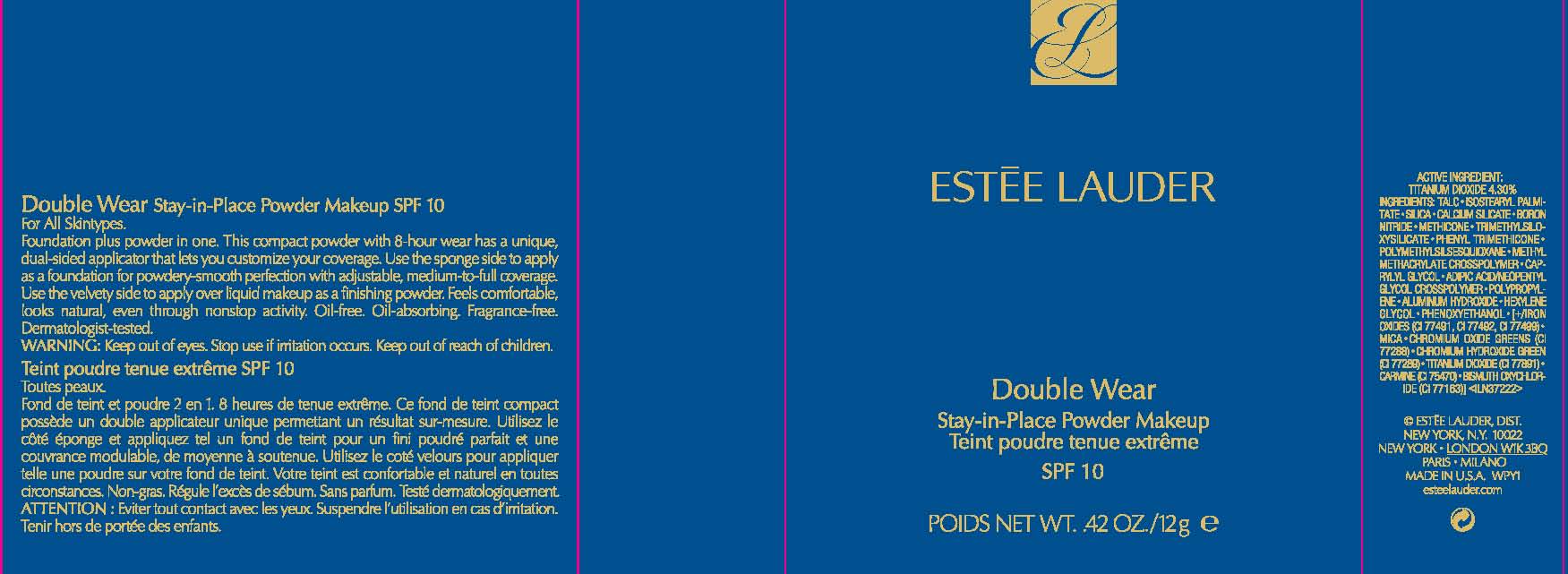 DRUG LABEL: DOUBLE WEAR
NDC: 11559-729 | Form: POWDER
Manufacturer: ESTEE LAUDER INC
Category: otc | Type: HUMAN OTC DRUG LABEL
Date: 20111004

ACTIVE INGREDIENTS: TITANIUM DIOXIDE 4.0 g/100 g
INACTIVE INGREDIENTS: TALC; SILICON DIOXIDE; CALCIUM SILICATE; BORON NITRIDE; PHENYL TRIMETHICONE; POLYMETHYLSILSESQUIOXANE (11 MICRONS); CAPRYLYL GLYCOL; ALUMINUM HYDROXIDE; HEXYLENE GLYCOL; PHENOXYETHANOL; FERRIC OXIDE RED; MICA; CHROMIC OXIDE; COCHINEAL; BISMUTH OXYCHLORIDE

ACTIVE INGREDIENT: TITANIUM DIOXIDE 4.4%

INDICATIONS AND USAGE

INACTIVE INGREDIENTS: TALC [] ISOSTEARYL PALMITATE [] SILICA [] CALCIUM SILICATE [] BORON NITRIDE [] METHICONE [] TRIMETHYLSILOXYSILICATE [] PHENYL TRIMETHICONE [] POLYMETHYLSILSESQUIOXANE [] METHYL METHACRYLATE CROSSPOLYMER [] CAPRYLYL GLYCOL [] ADIPIC ACID/NEOPENTYL GLYCOL CROSSPOLYMER [] POLYPROPYLENE [] HEXYLENE GLYCOL [] PHENOXYETHANOL [] [+/- IRON OXIDES (CI 77491, CI 77492, CI 77499) [] MICA [] CHROMIUM OXIDE GREENS (CI 77288) [] CHROMIUM HYDROXIDE GREEN (CI 77289) [] CARMINE (CI 75470) [] BISMUTH OXYCHLORIDE (CI 77163) [] TITANIUM DIOXIDE (CI 77891)]

WARNINGS

WARNING: KEEP OUT OF EYES. STOP USE IF IRRITATION OCCURS. KEEP OUT OF REACH OF CHILDREN.

PACKAGE LABEL

ESTEE LAUDER

DOUBLE WEAR

STAY-IN-PLACE POWDER MAKEUP
SPF 10
NET WT. 0.42 OZ/ 12 g
Estee Lauder Dist.
New York, NY 10022